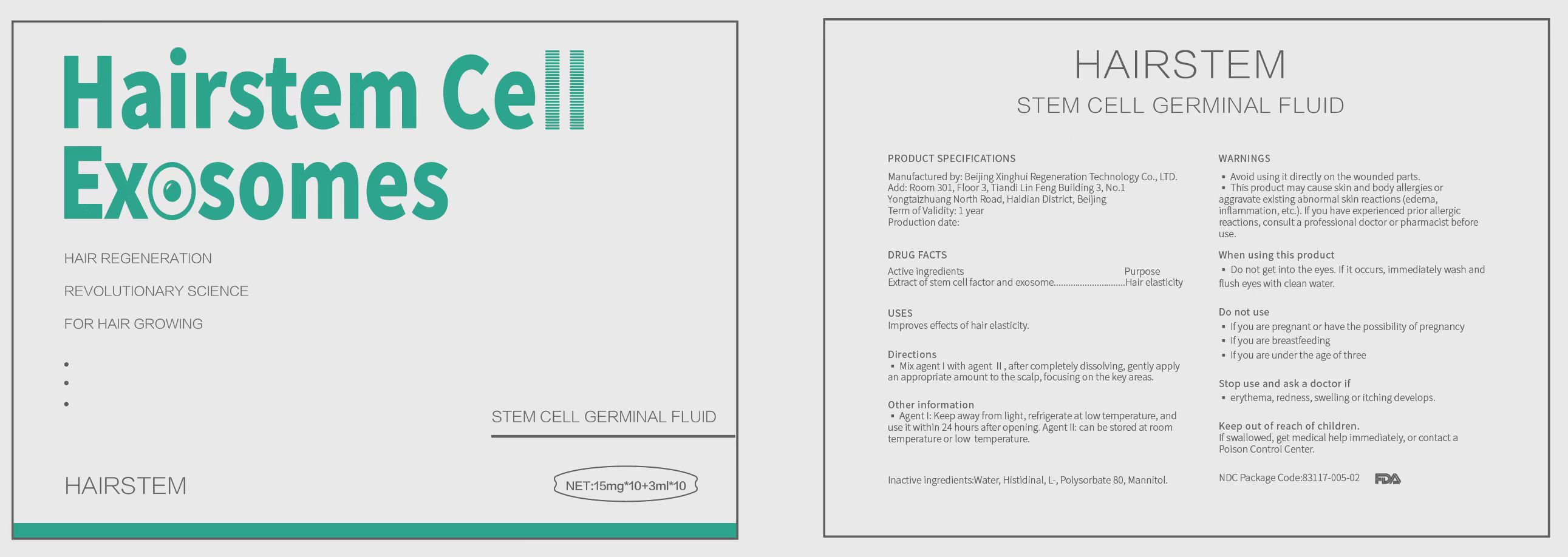 DRUG LABEL: Hairstem Cell Exosomes
NDC: 83117-005 | Form: POWDER, FOR SOLUTION
Manufacturer: Beijing Xinghui Regeneration Technology Co., LTD.
Category: otc | Type: HUMAN OTC DRUG LABEL
Date: 20230406

ACTIVE INGREDIENTS: ALLOGENEIC HUMAN UMBILICAL CORD-DERIVED MESENCHYMAL STEM CELLS 15 mg/3 mL
INACTIVE INGREDIENTS: MANNITOL 0.135 mL/3 mL; WATER 2.85 mL/3 mL; HISTIDINAL, L- 0.009 mL/3 mL; POLYSORBATE 80 0.006 mL/3 mL

Stem Cell Germinal Fluid

ACTIVE INGREDIENT

ALLOGENEIC HUMAN UMBILICAL CORD-DERIVED MESENCHYMAL STEM CELLS (MSCS) EXOSOMES.

WARNINGS

1.In the process of using this product, if the application site has abnormal symptoms or side effects such as erythema, redness, swelling or itching due to direct light, seek medical advice and consult a professional doctor immediately.
2.Avoid using it on wounds.
3.Keep the product out of reach of children.
4.If it accidentally gets into the eyes, immediately wash and flush eyes with clean water.
5.This product may cause skin and body allergies or aggravate existing abnormal skin reactions (edema, inflammation, etc.). If you have experienced prior allergic reactions, consult a professional doctor or pharmacist before use.

Keep out of reach of children. If swallowed, get medical help immediately, or contact a Poison Control Center.

PURPOSE

Improves effects of hair elasticity

Stop use and ask a doctor if erythema, redness, swelling or itching develops.

DOSAGE AND ADMINISTRATION

Mix agent I with agent Ⅱ, after completely dissolving, gently apply an appropriate amount to the scalp, focusing on the key areas.

Once every three days.

DO NOT USE

• If you are pregnant or have the possibility of pregnancy
• If you are breastfeeding
• If you are under the age of three

STORAGE AND HANDLING

Agent I: Keep away from light, refrigerate at low temperature, and use it within 24 hours after opening. Agent II: Can be stored at room temperature or low temperature.

INDICATIONS AND USAGE

Improves effects of hair elasticity.

Mix agent Ⅰwith agent Ⅱ, after completely dissolving, gently apply an appropriate amount to the scalp, focusing on the key areas.

INACTIVE INGREDIENT

water, mannitol, L-histidine, Tween-80